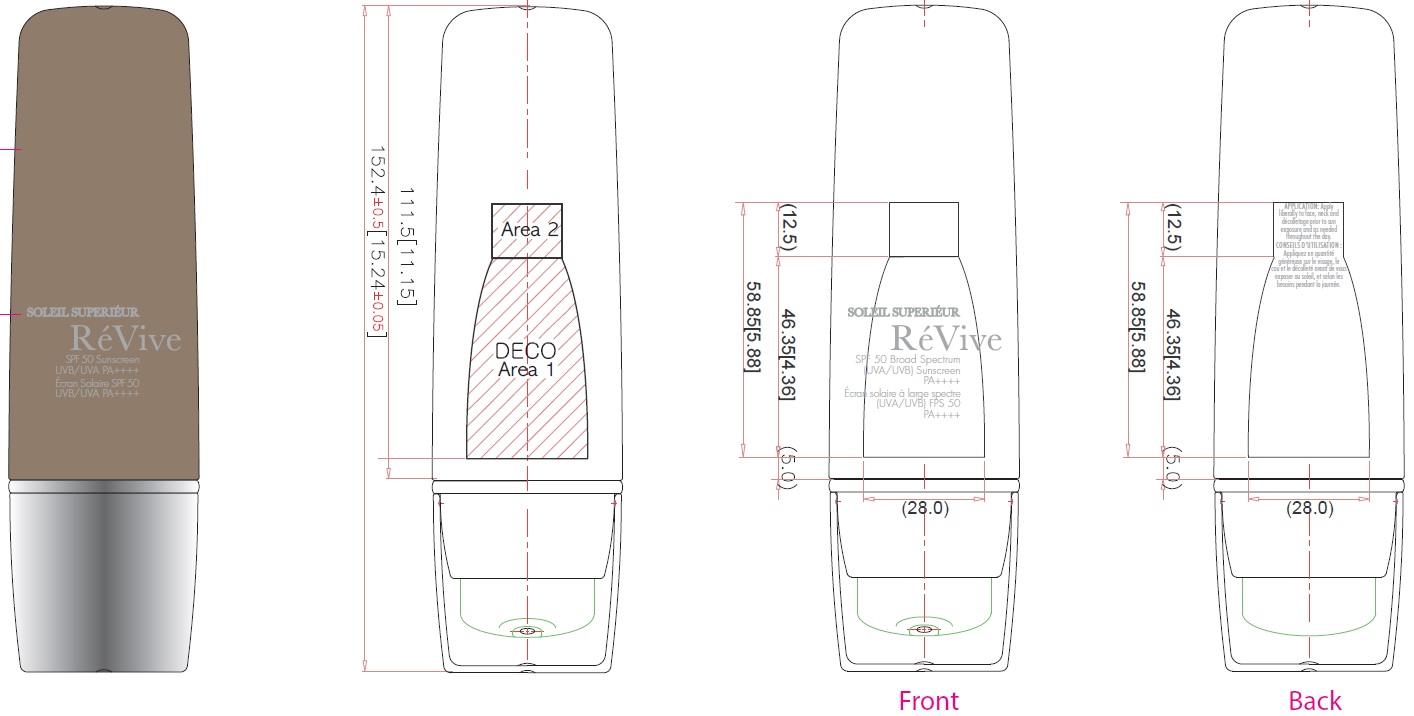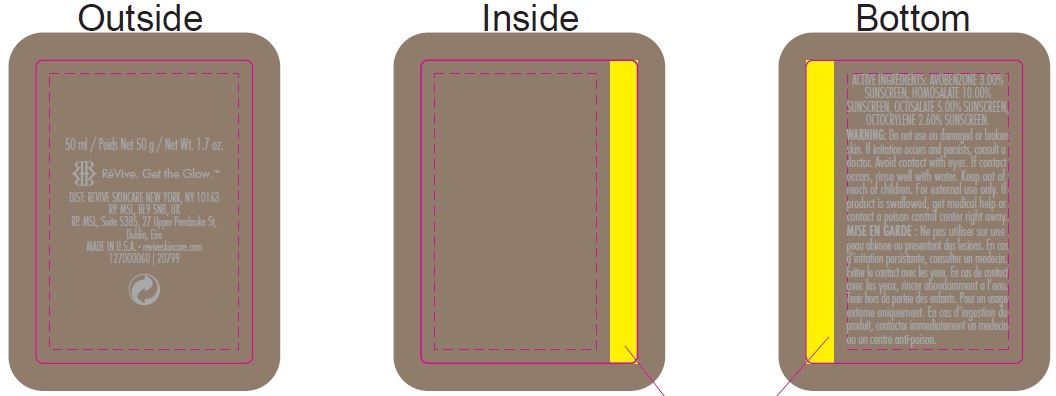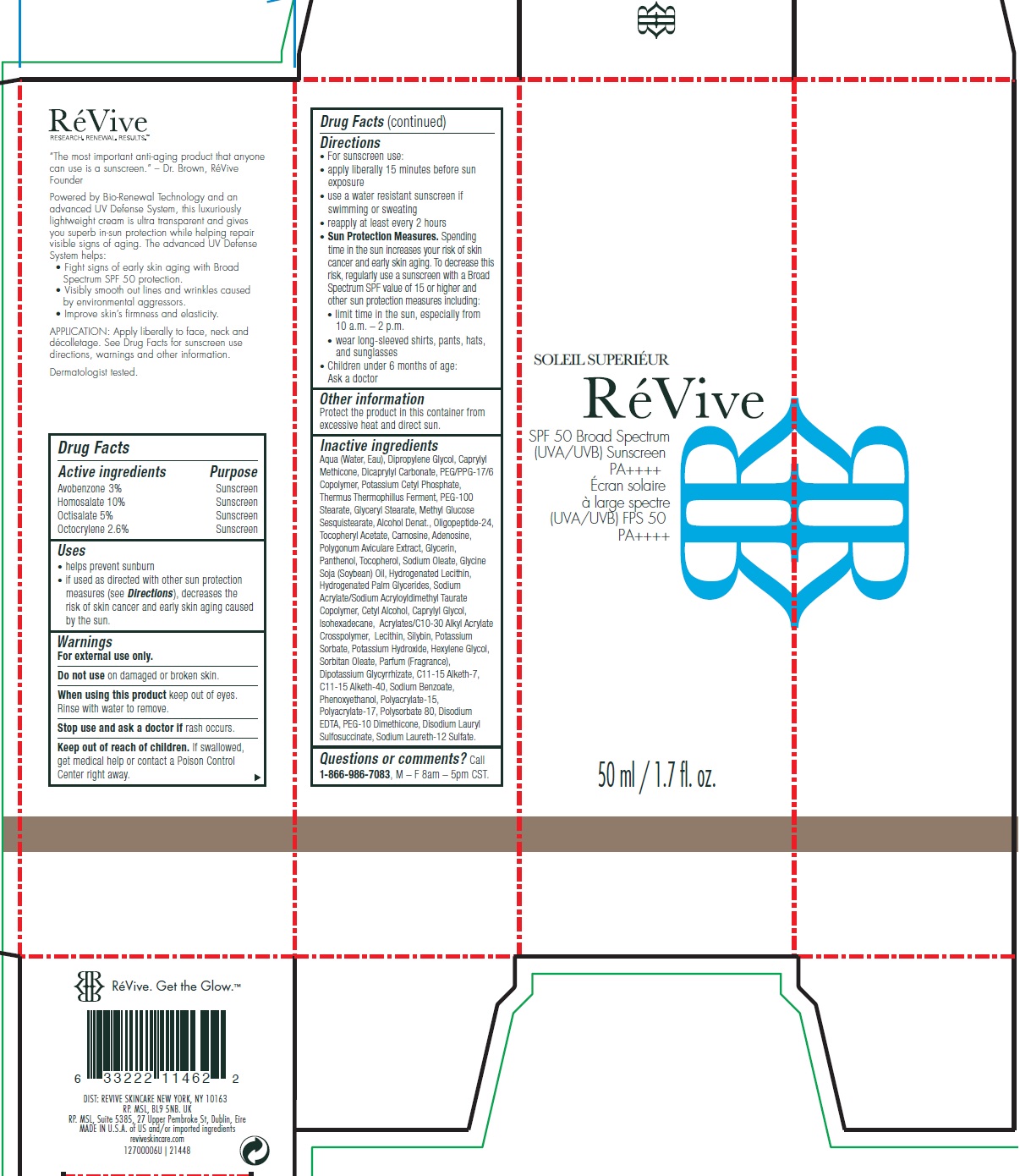 DRUG LABEL: Soleil Superieur Broad Spectrum SPF 50 Sunscreen US
NDC: 82691-146 | Form: CREAM
Manufacturer: RV Skincare LLC
Category: otc | Type: HUMAN OTC DRUG LABEL
Date: 20231106

ACTIVE INGREDIENTS: AVOBENZONE 30 mg/1 mL; HOMOSALATE 100 mg/1 mL; OCTISALATE 50 mg/1 mL; OCTOCRYLENE 26 mg/1 mL
INACTIVE INGREDIENTS: WATER; DIPROPYLENE GLYCOL; CAPRYLYL TRISILOXANE; DICAPRYLYL CARBONATE; PEG/PPG-17/6 COPOLYMER; POTASSIUM CETYL PHOSPHATE; THERMUS THERMOPHILUS LYSATE; PEG-100 STEARATE; GLYCERYL MONOSTEARATE; METHYL GLUCOSE SESQUISTEARATE; ALCOHOL; .ALPHA.-TOCOPHEROL ACETATE; CARNOSINE; ADENOSINE; POLYGONUM AVICULARE TOP; GLYCERIN; PANTHENOL; TOCOPHEROL; SODIUM OLEATE; SOYBEAN OIL; HYDROGENATED PALM GLYCERIDES; CETYL ALCOHOL; CAPRYLYL GLYCOL; ISOHEXADECANE; SILIBININ; POTASSIUM SORBATE; POTASSIUM HYDROXIDE; HEXYLENE GLYCOL; SORBITAN MONOOLEATE; GLYCYRRHIZINATE DIPOTASSIUM; SODIUM BENZOATE; PHENOXYETHANOL; POLYSORBATE 80; EDETATE DISODIUM ANHYDROUS; DISODIUM LAURYL SULFOSUCCINATE; SODIUM LAURETH-12 SULFATE

Soleil Superieur Broad Spectrum SPF 50 Sunscreen US

Active ingredients

Avobenzone 3%

Homosalate 10%

Octisalate 5%

Octocrylene 2.6%

Purpose

Sunscreen

Uses

• helps prevent sunburn

• if used as directed with other sun protection measures (see), decreases the risk of skin cancer and early skin aging caused by the sun. Directions

Warnings

For external use only.

Do not use

on damaged or broken skin.

When using this product

keep out of eyes. Rinse with water to remove.

Stop use and ask a doctor if

rash occurs.

Keep out of reach of children.

If swallowed, get medical help or contact a Poison Control Center right away.

Directions

• For sunscreen use: • apply liberally 15 minutes before sun exposure • use a water resistant sunscreen if swimming or sweating • reapply at least every 2 hours • Spending time in the sun increases your risk of skin cancer and early skin aging. To decrease this risk, regularly use a sunscreen with a Broad Spectrum SPF value of 15 or higher and other sun protection measures including: • limit time in the sun, especially from 10 a.m. – 2 p.m. • wear long-sleeved shirts, pants, hats, and sunglasses • Children under 6 months of age: Ask a doctor
Sun Protection Measures.

Other information

Protect the product in this container from excessive heat and direct sun.

Inactive ingredients:

Aqua (Water, Eau), Dipropylene Glycol, Caprylyl Methicone, Dicaprylyl Carbonate, PEG/PPG-17/6 Copolymer, Potassium Cetyl Phosphate, Thermus Thermophillus Ferment, PEG-100 Stearate, Glyceryl Stearate, Methyl Glucose Sesquistearate, Alcohol Denat., Oligopeptide-24, Tocopheryl Acetate, Carnosine, Adenosine, Polygonum Aviculare Extract, Glycerin, Panthenol, Tocopherol, Sodium Oleate, Glycine Soja (Soybean) Oil, Hydrogenated Lecithin, Hydrogenated Palm Glycerides, Sodium Acrylate/Sodium Acryloyldimethyl Taurate Copolymer, Cetyl Alcohol, Caprylyl Glycol, Isohexadecane, Acrylates/C10-30 Alkyl Acrylate Crosspolymer, Lecithin, Silybin, Potassium Sorbate, Potassium Hydroxide, Hexylene Glycol, Sorbitan Oleate, Parfum (Fragrance), Dipotassium Glycyrrhizate, C11-15 Alketh-7, C11-15 Alketh-40, Sodium Benzoate, Phenoxyethanol, Polyacrylate-15, Polyacrylate-17, Polysorbate 80, Disodium EDTA, PEG-10 Dimethicone, Disodium Lauryl Sulfosuccinate, Sodium Laureth-12 Sulfate.

Questions or comments?

Call , M – F 8am – 5pm CST. 1-866-986-7083